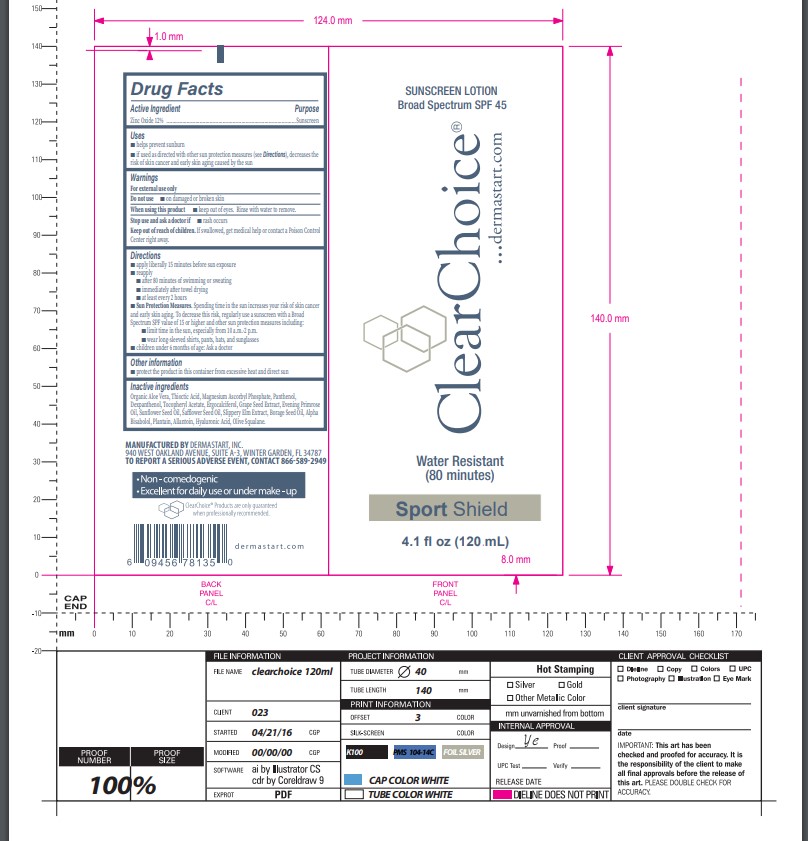 DRUG LABEL: ClearChoice Sport Shield
NDC: 83722-000 | Form: LOTION
Manufacturer: Dermastart Inc.
Category: otc | Type: HUMAN OTC DRUG LABEL
Date: 20231023

ACTIVE INGREDIENTS: ZINC OXIDE 120 mg/1 mL
INACTIVE INGREDIENTS: ALOE VERA WHOLE; ALPHA LIPOIC ACID; MAGNESIUM ASCORBYL PHOSPHATE; PANTHENOL; DEXPANTHENOL; .ALPHA.-TOCOPHEROL ACETATE, DL-; ERGOCALCIFEROL; VITIS VINIFERA SEED; EVENING PRIMROSE OIL; SUNFLOWER OIL; SAFFLOWER SEED OIL POLYGLYCERYL-6 ESTERS; BORAGE SEED OIL; .ALPHA.-BISABOLOL, (+/-)-; MUSA X PARADISIACA LEAF; ALLANTOIN; HYALURONIC ACID

ClearChoice Sport Shield

Active Ingredient

Zinc Oxide 12%

Purpose

Sunscreen

Uses

- helps prevent sunburn
- if used as directed with other sun protection measures (see Directions), decreases the risk of skin cancer and early skin aging caused by the sun

Warnings

For external use only

Do not use

- on damaged or broken skin

When using this product

- keep out of eyes. Rinse with water to remove.

Stop use and ask a doctor if

- rash occurs

Keep out of reach of children

If swallowed, get medical help or contact a Poison Control Center right away.

Directions

- apply liberally 15 minutes before sun exposure
- reapply
- after 80 minutes of swimming or sweating
- immediately after towel drying
- at least every 2 hours
- Sun Protection Measures. Spending time in the sun increases your risk of skin cancer and early skin aging. To decrease the risk, regularly use a sunscreen with a Broad Spectrum SPF value of 15 or higher and other sun protection measures including:
- limit time in the sun, especially from 10a.m.-2p.m.
- wear long-sleeved shirts, pants, hats, and sunglasses
- children under 6 months of age: Ask a doctor

Other Information

- protect the product in this container from excessive heat and direct sun

Inactive Ingredients

Organic Aloe Vera, Thioctic Acid, Magnesium Ascorbyl Phosphate, Panthenol, Dexpanthenol, Tocopheryl Acetate, Ergocalciferol, Grape Seed Extract, Evening Primrose Oil, Sunflower Seed Oil, Safflower Seed Oil, Slippery Elm Extract, Borage Seed Oil, Alpha Bisabolol, Plantain, Allantoin, Hyaluronic Acid, Olive Squalane.